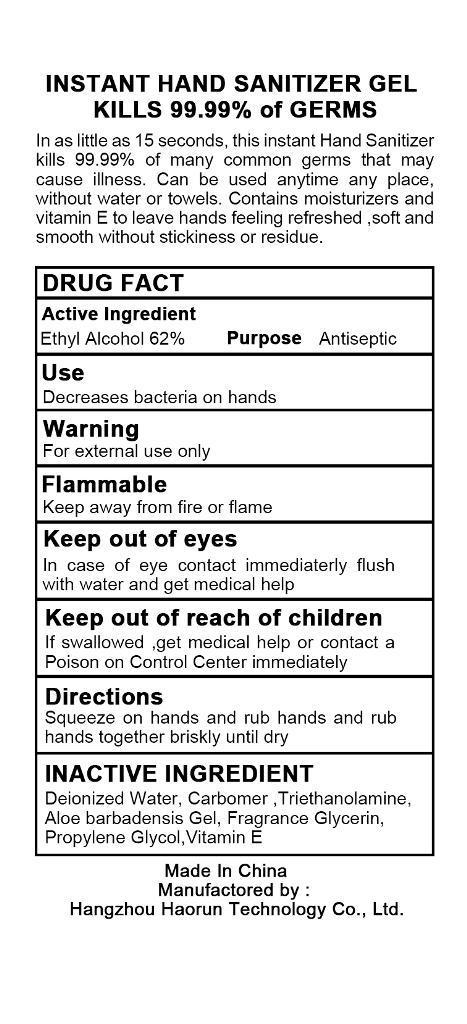 DRUG LABEL: HAND SANITIZER
NDC: 57817-200 | Form: GEL
Manufacturer: Hangzhou Haorun Technology CO.,LTD.
Category: otc | Type: HUMAN OTC DRUG LABEL
Date: 20130329

ACTIVE INGREDIENTS: ALCOHOL 62 mL/100 mL
INACTIVE INGREDIENTS: WATER; CARBOMER 940; TRIETHANOLAMINE BENZOATE; ALOE; Glycerin; PROPYLENE GLYCOL; TOCOPHEROL

INSTANT HAND SANITIZER GEL DRUG FACT

KILLS 99.99% of GERMS

In as little as 15 seconds, this instant Hand Sanitizer kills 99.99% of many common germs that may cause illness. Can be used anytime any place, without water or towels. Contains moisturizers and vitamin E to leave hands feeling refreshed ,soft and smooth without stickiness or residue.

Active Ingredient

Ethyl Alcohol 62%

Purpose

Antiseptic

Use

Decreases bacteria on hands

Warning

For external use only
Flammable
Keep away from fire or flame
Keep out of eyes
In case of eye contact immediaterly flush with water and get medical help
Keep out of reach of children
If swallowed ,get medical help or contact a Poison on Control Center immediately

Keep out of reach of children

Directions

Squeeze ont oh ands and rub hands and rub hands together briskly until dry

INACTIVE INGREDIENT

Deionized Water, Carbomer ,Triethanolamine, Aloe barbadensis Gel, Fragrance Glycerin,
Propylene Glycol,Vitamin E